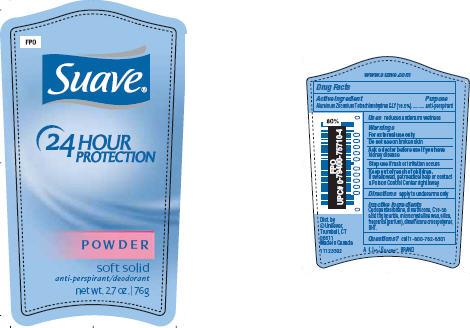 DRUG LABEL: Suave Powder
NDC: 64942-0747 | Form: STICK
Manufacturer: Conopco Inc. d/b/a Unilever
Category: otc | Type: HUMAN OTC DRUG LABEL
Date: 20100325

ACTIVE INGREDIENTS: Aluminum Zirconium Tetrachlorohydrex GLY 18.5 g/100 g

Suave Powder Antiperspirant and Deodorant PDP and drug facts

Active ingredient Purpose

Aluminum Zirconium Tetrachlorohydrex GLY(18.5%)............anti-perspirant

Warning
For external use only

Do not use on broken skin

Ask a doctor before use if you have kidney disease

Stop use if rash or irritation occurs

Keep out of reach of children. If swallowed, get medical help or contact a Poison Control Center right away.

Inactive ingredients

Cyclopentasiloxane, dimethicone, C18-36 acid triglyceride, microcrystalline wax, silica, fragrance (parfum), dimethicone crosspolymer, BHT.

Questions? call 1-800-782-8301

PACKAGE LABEL

PDP 2.7 oz